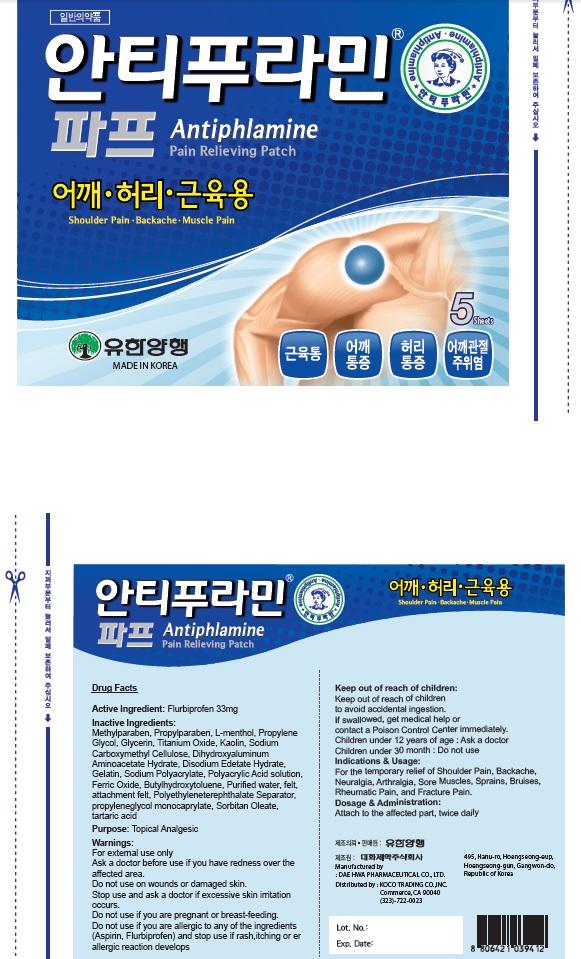 DRUG LABEL: Antiphlamine Pain Relieving
NDC: 69642-1300 | Form: PATCH
Manufacturer: HANUL TRADING CO., LTD.
Category: otc | Type: HUMAN OTC DRUG LABEL
Date: 20151013

ACTIVE INGREDIENTS: Flurbiprofen 33 mg/5 1
INACTIVE INGREDIENTS: Methylparaben; Propylparaben

ACTIVE INGREDIENT

Active Ingredient: Flurbiprofen 33mg

INACTIVE INGREDIENT

Inactive Ingredients: Methylparaben, Propylparaben, L-menthol, Propylene Glycol, Glycerin, Titanium Oxide, Kaolin, Sodium Carboxymethyl Cellulose, Dihydroxyaluminum Aminoacetate Hydrate, Disodium Edetate Hydrate, Gelatin, Sodium Polyacrylate, Polyacrylic Acid solution, Ferric Oxide, Butylhydroxytoluene, Purified water, felt, attachment felt, Polyethyleneterephthalate Separator, propyleneglycol monocaprylate, Sorbitan Oleate, tartaric acid

PURPOSE

Purpose: Topical Analgesic

WARNINGS

Warnings: For external use only Ask a doctor before use if you have redness over the affected area. Do not use: on wounds or damaged skin. Stop use and ask a doctor if excessive skin irritation occurs. Do not use if you are pregnant or breast feading. Do not use if you are allergic to any of the ingredients(Aspirin, Flurbiprofen) and stop use if rash, itching or allergic reaction develops.

Keep out of reach of children: Keep out of reach of children to avoid accidental ingestion. If swallowed, get medical help or contact a Poison Control Center immediately. Children under 12 years of age: Ask a doctor Children under 30 month: Do not use

INDICATIONS & USAGE

Indications & Usage: For the temporary relief of Shoulder Pain, Backache, Neuralgia, Arthralgia, Sore Muscles, Sprains, Bruises, Rheumatic Pain, and Fracture Pain.

DOSAGE & ADMINISTRATION

Dosage & Administration: Attach to the affected part, twice daily